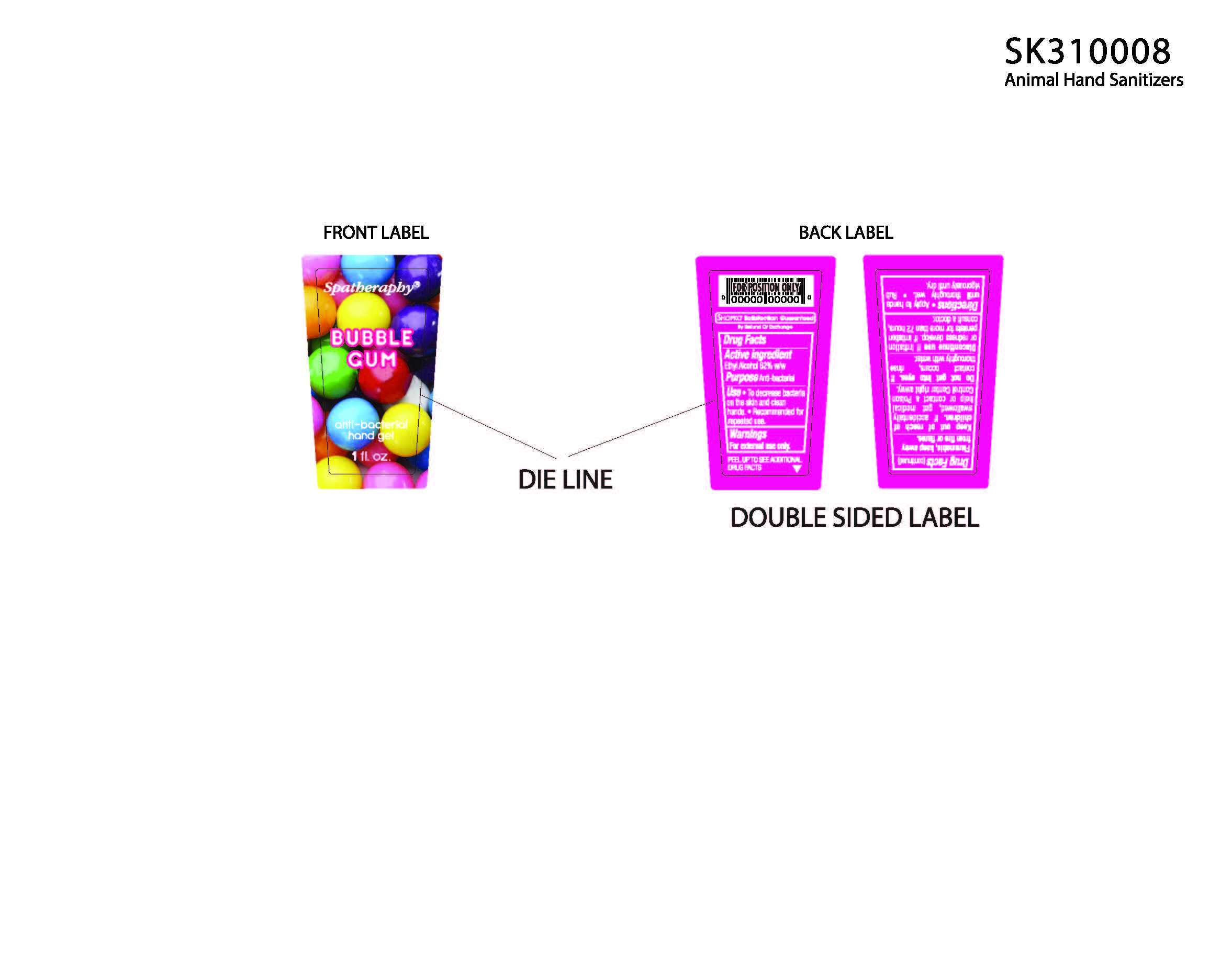 DRUG LABEL: Spatheraphy
                
                
                
                
                
NDC: 56136-005 | Form: LOTION
Manufacturer: Xiamen Olivee Daily Use Chemical Co., Ltd.
Category: otc | Type: HUMAN OTC DRUG LABEL
Date: 20130925

ACTIVE INGREDIENTS: ALCOHOL 18.6 mL/30 mL
INACTIVE INGREDIENTS: WATER; CARBOMER COPOLYMER TYPE A (ALLYL PENTAERYTHRITOL CROSSLINKED); TROLAMINE; POLYETHYLENE GLYCOL 2000; CASTOR OIL; D&C RED NO. 33; FD&C RED NO. 4; FD&C YELLOW NO. 5; FD&C BLUE NO. 1

Drug Facts

Inactive Ingredients

Water, Acrylates/C10-30 Alkyl Acrylate Crosspolymer,

Triethonalamine, Fragrance, PEG-40 Hydrogenated

Castor Oil, May contain:

D C Red 33, FD C Red 4, FD C Yellow 5, FD C Blue 1

Active Ingredient

Alcohol Denat 62 % w/w

Purpose

Antibacterial

Use

-To decrease bacteria on the skin and clean hands

-Recommended for repeated use

Warnings

For external use only

Keep out of reach of children.

If accidentally swallowed, get medical help or

contact a Poison Control Center right away.

STOP USE

Discontinue use if irritation or redness develop. If irritation persists

for more than 72 hours, consult a doctor.

Do not get into eye. If contact occurs, rinse thoroughly with water.

DOSAGE AND ADMINISTRATION

Directions - Apply to hands until thoroughly wet - Rub

vigorously until dry.